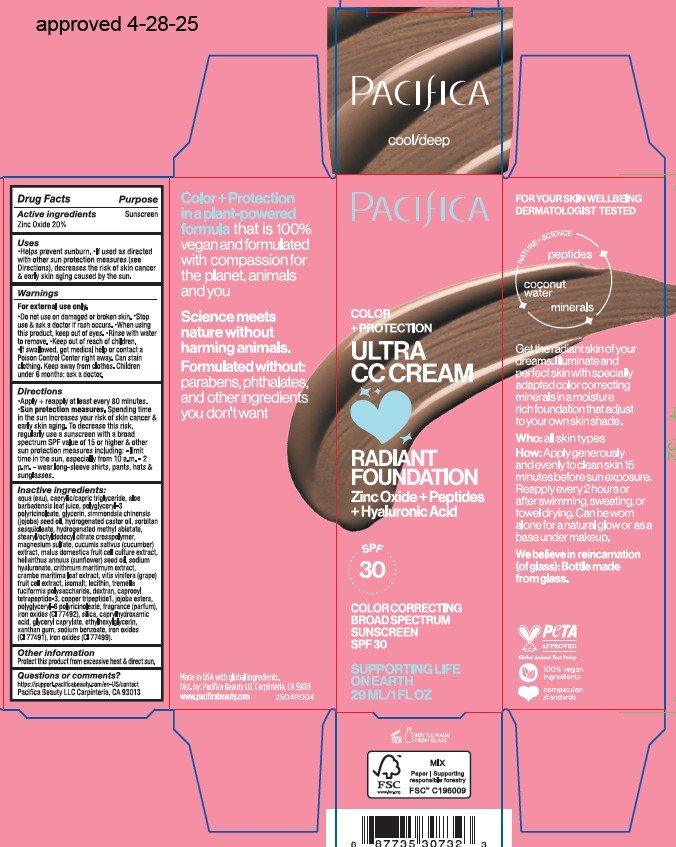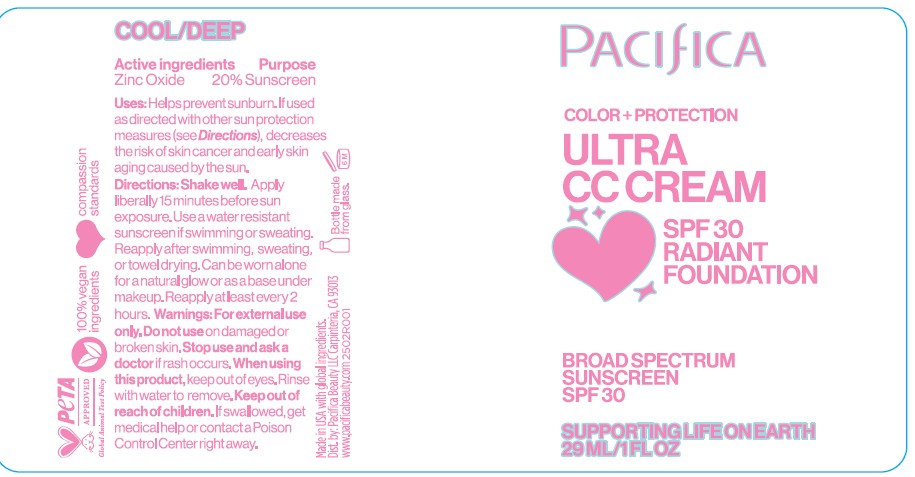 DRUG LABEL: Zinc Oxide
NDC: 61197-312 | Form: CREAM
Manufacturer: Pacifica Beauty, LLC
Category: otc | Type: HUMAN OTC DRUG LABEL
Date: 20250610

ACTIVE INGREDIENTS: ZINC OXIDE 20 mg/100 mL
INACTIVE INGREDIENTS: CAPRYLIC/CAPRIC TRIGLYCERIDE; SIMMONDSIA CHINENSIS (JOJOBA) SEED OIL; GLYCERIN; HYDROGENATED CASTOR OIL; SORBITAN SESQUIOLEATE; SILICA; GLYCERYL CAPRYLATE; MAGNESIUM SULFATE; CRITHMUM MARITIMUM; COPPER TRIPEPTIDE-1; WATER; ETHYLHEXYLGLYCERIN; CUCUMIS SATIVUS (CUCUMBER) FRUIT; MALUS DOMESTICA FLOWER; CRAMBE MARITIMA LEAF; POLYGLYCERYL-6 POLYRICINOLEATE; CI 77492; CAPRYLHYDROXAMIC ACID; POLYGLYCERYL-3 RICINOLEATE; SODIUM HYALURONATE; VITIS VINIFERA FRUIT OIL; ISOMALT; LECITHIN, SOYBEAN; TREMELLA FUCIFORMIS WHOLE; DEXTRAN 1; CAPROOYL TETRAPEPTIDE-3; HYDROLYZED JOJOBA ESTERS; XANTHAN GUM; SODIUM BENZOATE; CI 77499; CI 77491; ALOE BARBADENSIS LEAF JUICE; HYDROGENATED METHYL ABIETATE; STEARYL/OCTYLDODECYL CITRATE CROSSPOLYMER; HELIANTHUS ANNUUS (SUNFLOWER) SEED OIL

Pacifica Ultra CC Cream Radiant Foundation SPF 30 Cool/Deep

Active ingredients

Zinc Oxide 20%

Purpose

Sunscreen

Uses

Helps prevent sunburn. If used as directed with other sun protection measures (see Directions), decreases the risk of skin cancer & early skin aging caused by the sun.

Warnings

For external use only. Do not use on damaged or broken skin. Stop use & ask a doctor if rash occurs. When using this product, keep out of eyes. Rinse with water to remove. Keep out of reach ofchildren. If swallowed, get medical help or contact a Poison Control Center right away. Can stain clothing. Keep away from clothes. Children under 6 months: ask a doctor.

Keep out of reach of children

Directions

Apply + reapply at least every 80 minutes. Sun protection measures. Spending time in the sun increases your risk of skin cancer & early skin aging. To decrease this risk, regularly use a sunscreen with a broad spectrum SPF value of 15 or higher & other sun rrpotection measures including: -limit time in the sun, especially from 10 a.m. - 2 p.m. -wear long-sleeve shirts, pants, hats & sunglasses.

Inactive ingredients

aqua (eau), caprylic/capric triglyceride, aloe barbadensis leaf juice, polyglyceryl-3 polyricinoleate, glycerin, simmondsia chinensis (jojoba) seed oil, hydrogenated castor oil, sorbitan sesquioleate, hydrogenated methyl abietate, stearyl/octyldodecyl citrate crosspolymer, magnesium sulfate, cucumis sativus (cucumber) extract, malus domestica fruit cell culture extract, helinathus annuus (sunflower) seed oil, sodium hyaluronate, crithmum maritimum extract, crame maritima leaf extract, vitis vinifera (grape) fruit cell extract, isomalt, lecithin, tremella fuciformis polysaccharide, dextran, caprooyl tetrapeptide-3, copper tripeptide-1, jojoba esters, polyglyceryl-6 polyricinoleate, fragrance (parfum), iron oxides (CI 77492), silica, caprylhydroxamic acid, glyceryl caprylate, ethylhexylglycerin, xanthan gum, sodium benzoate, iron oxides (CI 77491), iron oxides (CI 77499).

Other information

Protect this product from excessive heat & direct sun.

Questions or comments?

https://support.pacificabeauty.com/en-US/contact

Pacifica Beauty LLC Carpinteria, CA 93013